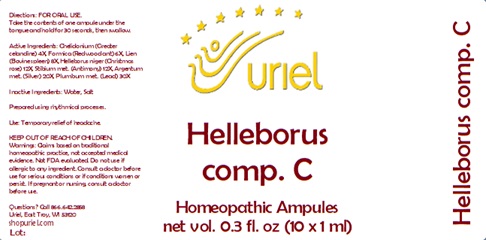 DRUG LABEL: Helleborus comp. C
NDC: 48951-5119 | Form: LIQUID
Manufacturer: Uriel Pharmacy Inc.
Category: homeopathic | Type: HUMAN OTC DRUG LABEL
Date: 20241217

ACTIVE INGREDIENTS: SILVER 20 [hp_X]/1 mL; LEAD 30 [hp_X]/1 mL; CHELIDONIUM MAJUS 4 [hp_X]/1 mL; FORMICA RUFA 6 [hp_X]/1 mL; BOS TAURUS SPLEEN 8 [hp_X]/1 mL; HELLEBORUS NIGER ROOT 12 [hp_X]/1 mL; ANTIMONY 12 [hp_X]/1 mL
INACTIVE INGREDIENTS: SODIUM CHLORIDE; WATER

Helleborus comp. C

INDICATIONS AND USAGE

Directions: FOR ORAL USE.

DOSAGE AND ADMINISTRATION

Take the contents of one ampule under the tongue and hold for 30 seconds, then swallow.

ACTIVE INGREDIENT

Active Ingredients: Chelidonium (Greater celandine) 4X, Formica (Red wood ant) 6X, Lien (Bovine spleen) 8X, Helleborus niger (Christmas rose) 12X, Stibium (Antimony) 12X, Argentum (Silver) 20X, Plumbum (Lead) 30X

Inactive Ingredients: Water, Salt

Prepared using rhythmical processes.

PURPOSE

Use: Temporary relief of headache.

KEEP OUT OF REACH OF CHILDREN.

WARNINGS

Warnings: Claims based on traditional homeopathic practice, not accepted medical evidence. Not FDA evaluated. Do not use if allergic to any ingredient. Consult a doctor before use for serious conditions or if conditions worsen or persist. If pregnant or nursing, consult a doctor before use.

Questions? Call 866.642.2858
Uriel, East Troy, WI 53120
shopuriel.com Lot: